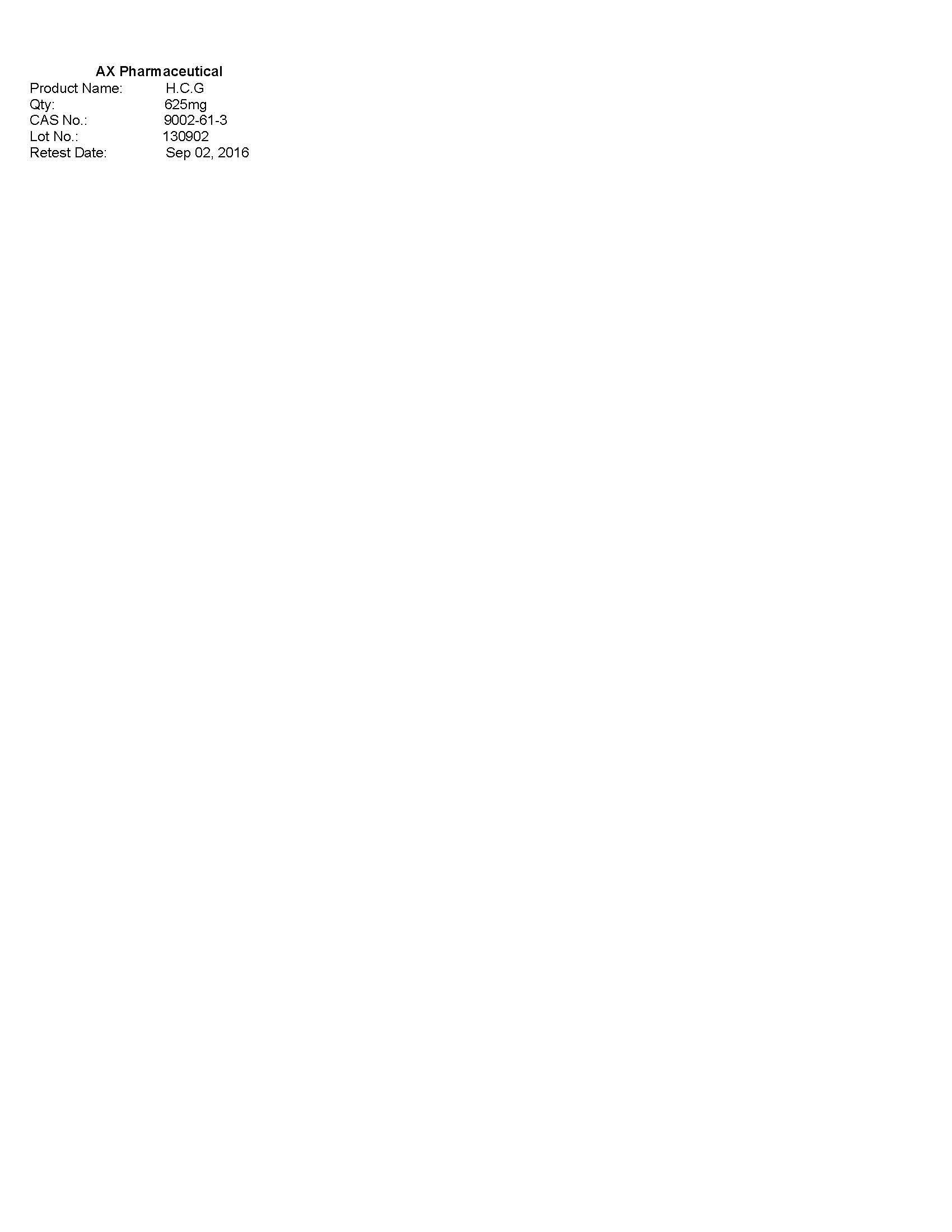 DRUG LABEL: AX Pharmaceutical
                
NDC: 62157-005 | Form: POWDER
Manufacturer: AX Pharmaceutical Corp
Category: other | Type: BULK INGREDIENT
Date: 20151204

ACTIVE INGREDIENTS: GONADOTROPHIN, CHORIONIC 6500 [iU]/1 mg
INACTIVE INGREDIENTS: WATER

Drug Facts